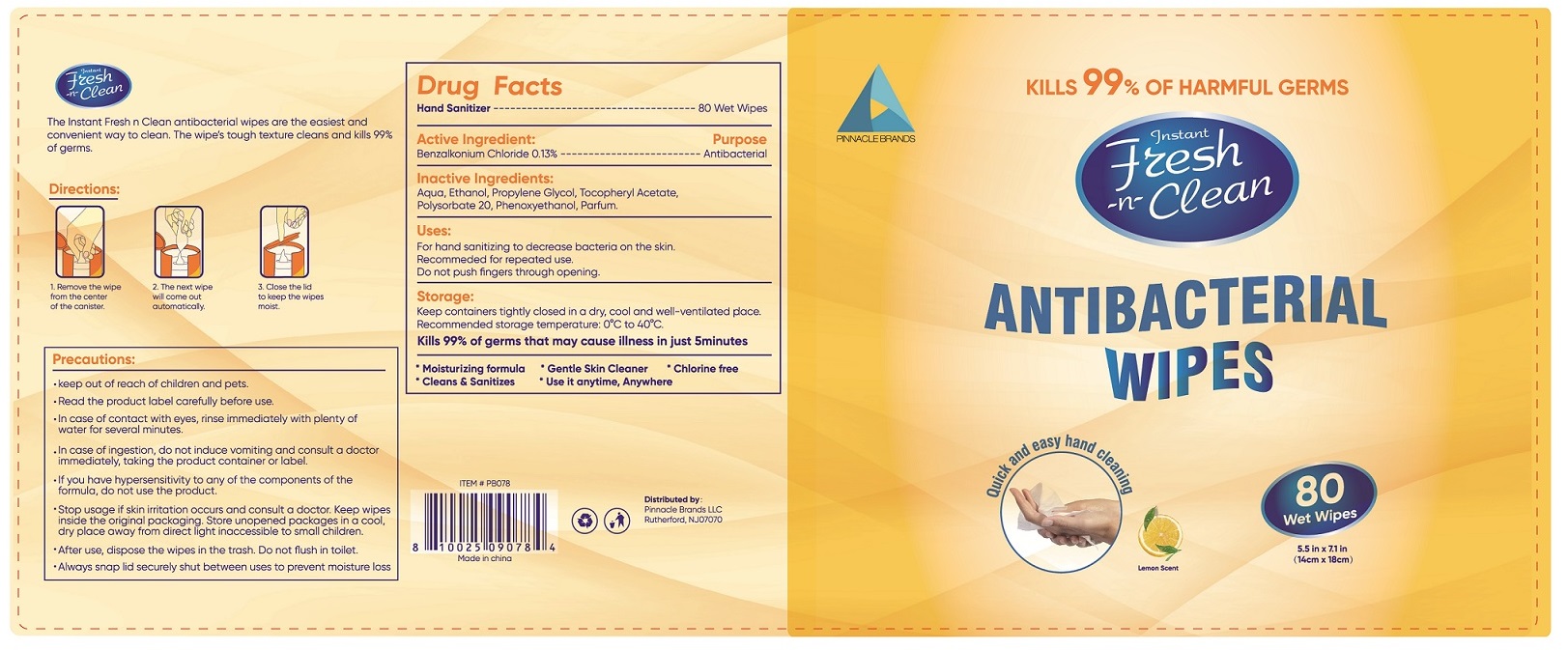 DRUG LABEL: Antibacterial Wet Wipes
NDC: 75662-081 | Form: CLOTH
Manufacturer: Ningbo Chenxing Daily Necessities Co., Ltd.
Category: otc | Type: HUMAN OTC DRUG LABEL
Date: 20200811

ACTIVE INGREDIENTS: BENZALKONIUM CHLORIDE 0.13 g/100 g
INACTIVE INGREDIENTS: ALCOHOL; .ALPHA.-TOCOPHEROL ACETATE; POLYSORBATE 20; WATER; PROPYLENE GLYCOL; FRAGRANCE LEMON ORC2001060; PHENOXYETHANOL

75662-081 Antibacterial Wet Wipes Ningbo Chenxing Daily Necessities Co., Ltd.

Active Ingredient(s)

Benzalkonium Chloride 0.13%. Purpose: Antibacterial

Purpose

Antibacterial, Wet Wipes

Use

For hand santizing to decrease bacteria on the skin.

Recommeded for repeated use.

Do not push fingers through opening.

Warnings

- keep out of reach of children and pets.
- Read the product label carefully before use.
- In case of contact with eyes, rinse immediately with plenty of water for several minutes.
- In case of ingestion, do not induce vomiting and consult a doctor immediately , taking the product container or label.
- If you have hypersensitivity to any of the components of the formula, do not use the product.
- Stop usage if skin irritation occurs and consult a doctor. Keep wipes inside the original packaging. Store unopened packages in a cool, dry place away from direct light inaccessible to small children.
  - After use, dispose the wipes in the trash. Do not flush in toilet.
  - Always snap lid securely shut between uses to prevent moisture loss.

Do not use

- in children less than 2 months of age
- on open skin wounds

When using this product keep out of eyes, ears, and mouth. In case of contact with eyes, rinse eyes thoroughly with water.
Stop use and ask a doctor if irritation or rash occurs. These may be signs of a serious condition.
Keep out of reach of children. If swallowed, get medical help or contact a Poison Control Center right away.

Stop use and ask a doctor if irritation or rash occurs. These may be signs of a serious condition.

Keep out of reach of children. If swallowed, get medical help or contact a Poison Control Center right away.

Directions

1.Remove the wipe from the center of the canister.

2.The next wipe will come out automatically.

3.Close the lid to keep the wipes moist.

Other information

Keep containers tightly closed in a dry, cool and well-ventilated place.

Recommended storage temperature: 0℃ to 40℃.

Kill 99% of germs that may cause illness in just 5 minutes.

Inactive ingredients

Aqua,Ethanol,Propylene Glycol,Tocopheryl Acetate,Polysorbate 20,Phenoxyethanol,Parfum

Package Label - Principal Display Panel

80 Wet Wipes NDC:75662-081-80